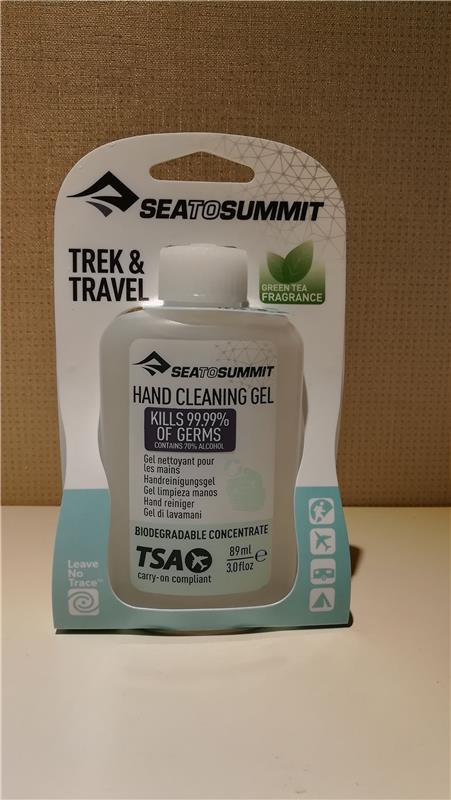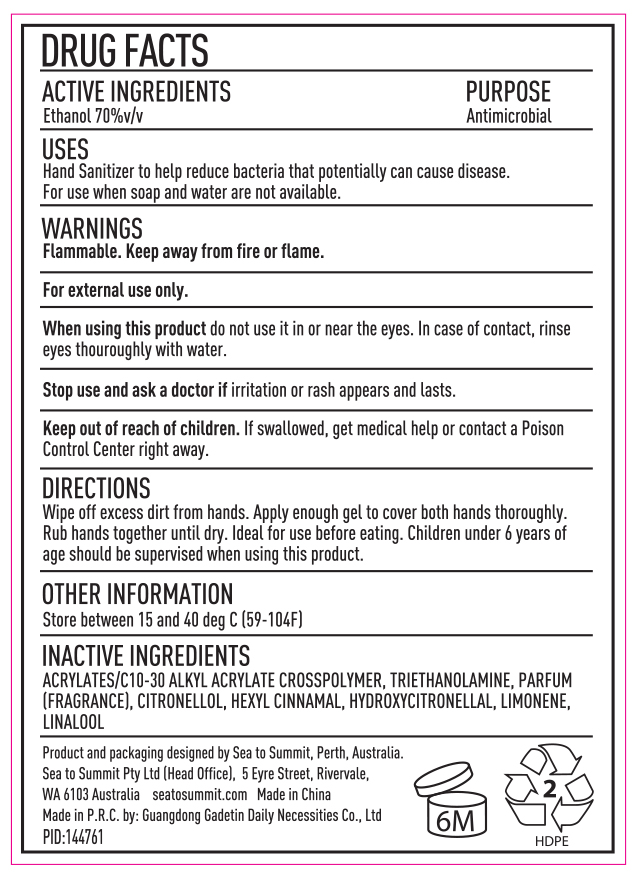 DRUG LABEL: Hand Cleaning Gel
NDC: 79238-1110 | Form: LIQUID
Manufacturer: Sea to Summit Pty Ltd
Category: otc | Type: HUMAN OTC DRUG LABEL
Date: 20211115

ACTIVE INGREDIENTS: ALCOHOL 70 mL/100 mL
INACTIVE INGREDIENTS: WATER 29.21 mL/100 mL; CARBOMER COPOLYMER TYPE A 0.35 mL/100 mL; TROLAMINE 0.34 mL/100 mL; GREEN TEA LEAF 0.1 mL/100 mL

Hand Sanitizer Gel 50ml; 100ml and 89ml